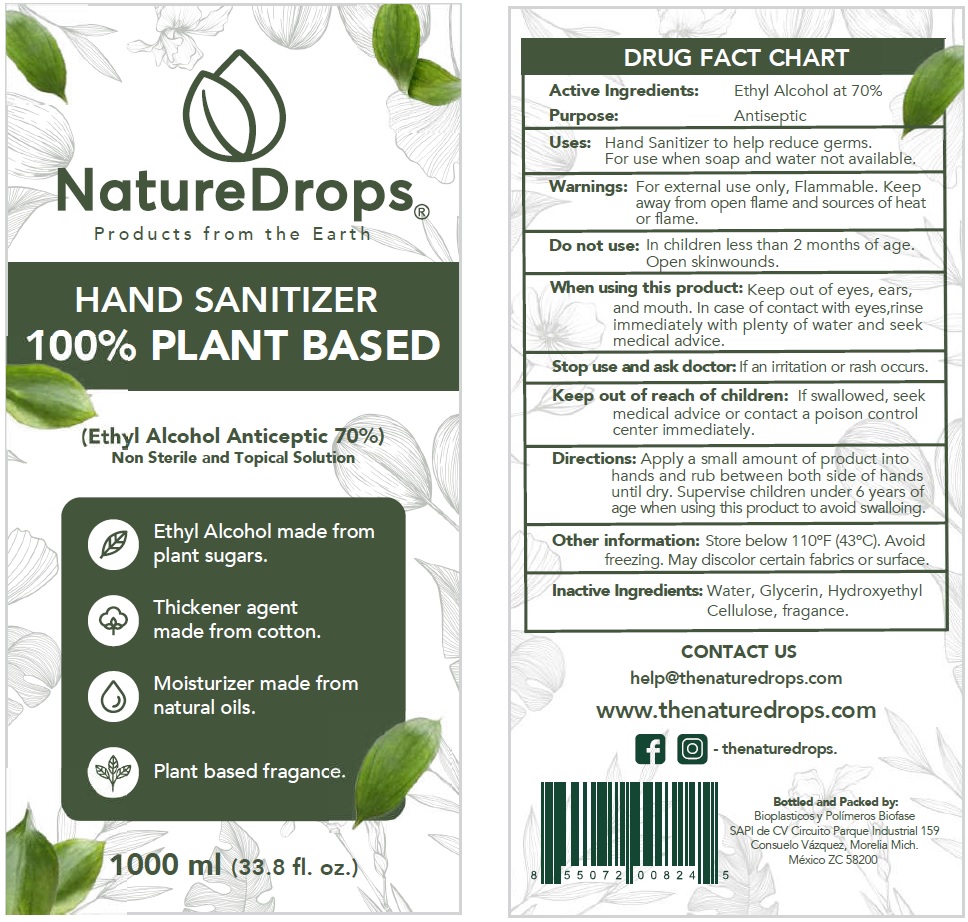 DRUG LABEL: Nature Drops Hand Sanitizer
NDC: 77452-001 | Form: LIQUID
Manufacturer: Bioplasticos y Polimeros BIOFASE, S.A.P.I. de C.V.
Category: otc | Type: HUMAN OTC DRUG LABEL
Date: 20200508

ACTIVE INGREDIENTS: ALCOHOL 0.7 mL/1 mL
INACTIVE INGREDIENTS: WATER; GLYCERIN; HYDROXYETHYL CELLULOSE, UNSPECIFIED

Nature Drops Hand Sanitizer

Active Ingredients:

Ethyl Alcohol at 70%

Purpose:

Antiseptic

Uses:

Hand Sanitizer to help reduce germs. For use when soap and water not available.

Warnings:

For external use only, Flammable. Keep away from open flame and sources of heat or flame.

Do not use:

In children less than 2 months of age. Open skinwounds.

When using this product:

Keep out of eyes, ears, and mouth. In case of contact with eyes,rinse immediately with plenty of water and seek medical advice.

Stop use and ask doctor:

If an irritation or rash occurs.

Keep out of reach of children:

If swallowed, seek medical advice or contact a poison control center immediately.

Directions:

Apply a small amount of product into hands and rub between both side of hands until dry. Supervise children under 6 years of age when using this product to avoid swalloing.

Other information:

Store below 110ºF (43ºC). Avoid freezing. May discolor certain fabrics or surface.

Inactive Ingredients:

Water, Glycerin, Hydroxyethyl Cellulose, fragance.